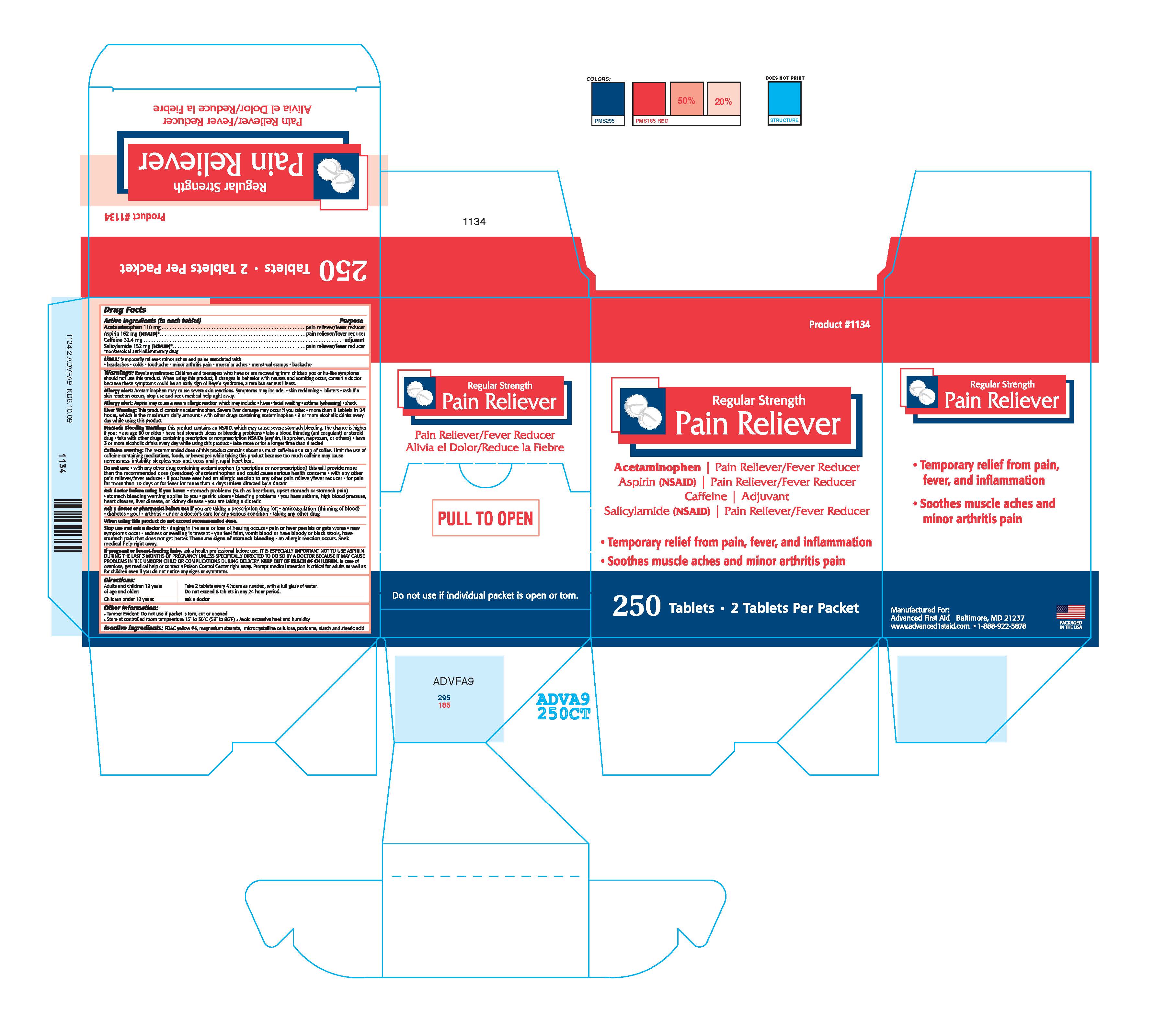 DRUG LABEL: PAIN RELIEVER
NDC: 67060-113 | Form: TABLET
Manufacturer: ADVANCED FIRST AID, INC.
Category: otc | Type: HUMAN OTC DRUG LABEL
Date: 20190531

ACTIVE INGREDIENTS: ACETAMINOPHEN 110 1/1 1; ASPIRIN 162 1/1 1; SALICYLAMIDE 152 1/1 1; CAFFEINE 32.4 1/1 1
INACTIVE INGREDIENTS: FD&C YELLOW NO. 6; MAGNESIUM STEARATE; CELLULOSE, MICROCRYSTALLINE; STARCH, CORN; STEARIC ACID

ACTIVE INGREDIENT IN EACH TABLET- ACETAMINOPHEN 110 MG, ASPIRIN 162 MG, CAFFEINE 32.4 MG, SALICYLAMIDE 152 MG

PURPOSE

PAIN RELIEVER/FEVER REDUCER

Uses:

temporarily relieves minor aches and pains associated with:

• headaches • colds • toothache • minor arthritis pain • muscular aches • menstrual cramps • backache

Warnings:

Reye's syndrome:

Children and teenagers who have or are recovering from chicken pox or flu-like symptoms should not use this product. When using this product, if changes in behaviour with nausea and vomiting occur, consult a doctor, because these symptoms could be an early sign of Reye's syndrome, a rare but serious illness.

Alergy Alert: Acetaminophen may cause severe skin reactions. Symptoms may include: • skin reddening • blisters • rash. If a skin reaction occurs, stop use and seek medical help right away.

Allergy Alert: Aspirin may cause a severe allergic reaction, which may include: • hives • facial swelling • asthma (wheezing) • shock

Liver Warning:

This product contains Acetaminophen. Severe liver damage may occur if you take:

• more than 8 tablets in 24 hours, which is the maximum daily amount

• with other drugs containing acetaminophen

• 3 or more alcoholic drinks every day while using this product

Stomach Bleeding Warning:

This product contains an NSAID, which may cause severe stomach bleeding. The chance is higher if you:

• are age 60 or older

• have had stomach ulcers or bleeding problems

• take a blood thinning (anticoagulant) or steroid drug

• take with other drugs containing prescription or nonprescription NSAIDs (aspirin, ibuprofen, naproxen, or others)

• have 3 or more alcoholic drinks every day while using this product

• take more or for a longer time than directed

Caffeine Warning:

The recommended dose of this product contains about as much caffeine as a cup of coffee. Limit the use of caffeine-containing medications, foods, or beverages while taking this product because too much caffeine may cause nervousness, irritability, sleeplessness, and, occasionally, rapid heart beat.

Do not use:

• with any other product containing acetaminophen (prescription or nonprescription). This will provide more than the recommended dose (overdose) of acetaminophen and could cause serious health concerns.

• with any other pain reliever/fever reducer

• if you are allergic to aspirin

• if you have ever had an allergic reaction to any other pain reliever/fever reducer

• for pain for more than 10 days or for fever for more than 3 days unless directed by a doctor

Ask doctor before using if you have:

• stomach problems (such as heartburn, upset stomach or stomach pain)

• stomach bleeding warning applies to you

• gastric ulcers • bleeding problems

• you have asthma, high blood pressure, heart disease, liver disease, or kidney disease

• you are taking a diuretic

Ask a doctor or pharmacist before use if you are taking a prescription drug for:

•anticoagulation (thinning of blood) • diabetes • gout • arthritis

• und a doctor's care for any serious condition

• taking any other drug

When using this product do not exceed recommended dose.

Stop use and ask a doctor if:

• ringing in the ears or loss of hearing occurs

• pain or fever persists or gets worse

• new symptoms occur

• redness or swelling is present

• you feel faint, vomit blood or have bloody or black stools, have stomach pain that does not get better. These are signs of stomach bleeding.

• an allergic reaction occurs.

Seek medical help right away.

PREGNANCY OR BREAST FEEDING

If pregnant or breast-feeding baby, ask a health professional before use. IT IS ESPECIALLY IMPORTANT NOT TO USE ASPIRIN

DURING THE LAST 3 MONTHS OF PREGNANCY UNLESS SPECIFICALLY DIRECTED TO DO SO BY A DOCTOR BECAUSE IT

MAY CAUSE PROBLEMS IN THE UNBORN CHILD OR COMPLICATIONS DURING DELIVERY.

KEEP OUT OF REACH OF CHILDREN

In case of overdose, get medical help or contact a Poison Control Center right away. Prompt medical attention is critical for

adults as well as for children even if you do not notice any signs or symptoms.

DOSAGE AND ADMINISTRATION

Adults and children 12 years of age and older:Take 2 tablets every 4 hours as

needed, with a full glass of water. Do not exceed 8 tablets in any 24 hour period.

Children under 12 years: ask a doctor.

INACTIVE INGREDIENT

FD&C yellow #6, magnesium stearate, microcrystalline cellulose, povidone, starch and stearic acid